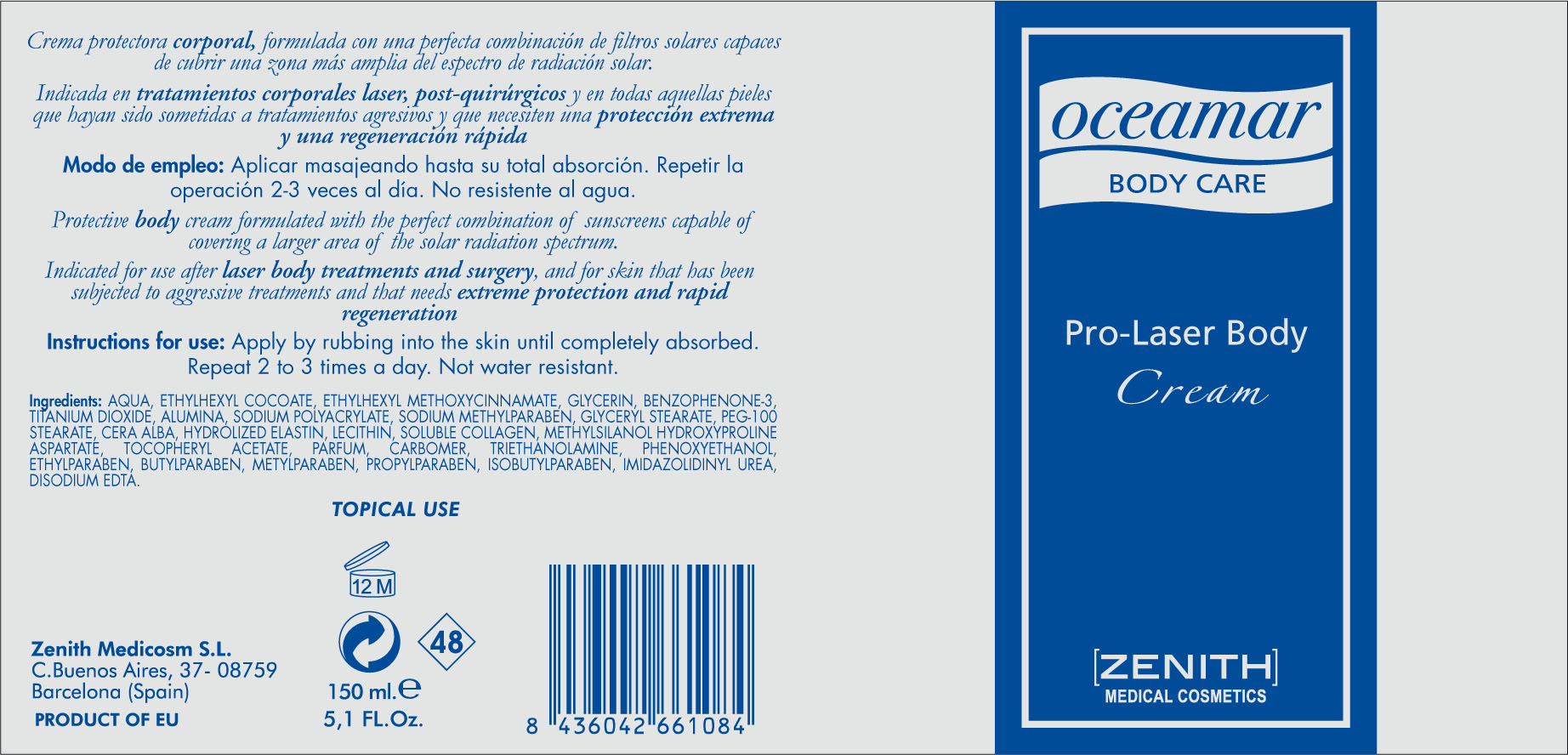 DRUG LABEL: PRO LASER
NDC: 42248-130 | Form: CREAM
Manufacturer: Zenith Medicosm SL
Category: otc | Type: HUMAN OTC DRUG LABEL
Date: 20120523

ACTIVE INGREDIENTS: OCTINOXATE 11.25 mL/150 mL; TITANIUM DIOXIDE 37.5 mL/150 mL; OXYBENZONE 9 mL/150 mL
INACTIVE INGREDIENTS: ALUMINUM OXIDE; PROPYLPARABEN; ALPHA-TOCOPHEROL ACETATE; COCONUT ACID; SODIUM POLYACRYLATE (8000 MW); METHYLPARABEN SODIUM; WATER; GLYCERYL MONOSTEARATE; PEG-100 STEARATE; WHITE WAX; HYDROGENATED SOYBEAN LECITHIN; GLYCERIN; TROLAMINE; ISOBUTYLPARABEN; HYDROLYZED ELASTIN, BOVINE, ALKALINE (1000 MW); CARBOMER 934; IMIDUREA; EDETATE DISODIUM; METHYLPARABEN; COLLAGEN, SOLUBLE, FISH SKIN; PHENOXYETHANOL; BUTYLPARABEN; ETHYLPARABEN; (2-CARBETHOXYETHYL)DIETHOXY(METHYL)SILANE; HYDROXYPROLINE; ASPARTIC ACID

Drug Facts

Active Ingredient

Octinoxate 7.5%

Titanium Dioxide 25%

Oxybenzone 6%

Description

PRO LASER BODY EMULSION

SPF 35

Protective body cream formulated with the perfect combination of sunscreens capable of covering a larger area of the solar radiation spectrum. Indicated for use after laser body treatments and surgery, and for skin that has been subjected to aggressive treatments and that needs extreme protection and rapid regeneration

Apply by rubbing into the skin until completely absorbed. Repeat 2 to 3 times a day. Not water resistant.

150ml. 5.1 fl. Oz

Warning

TOPICAL USE